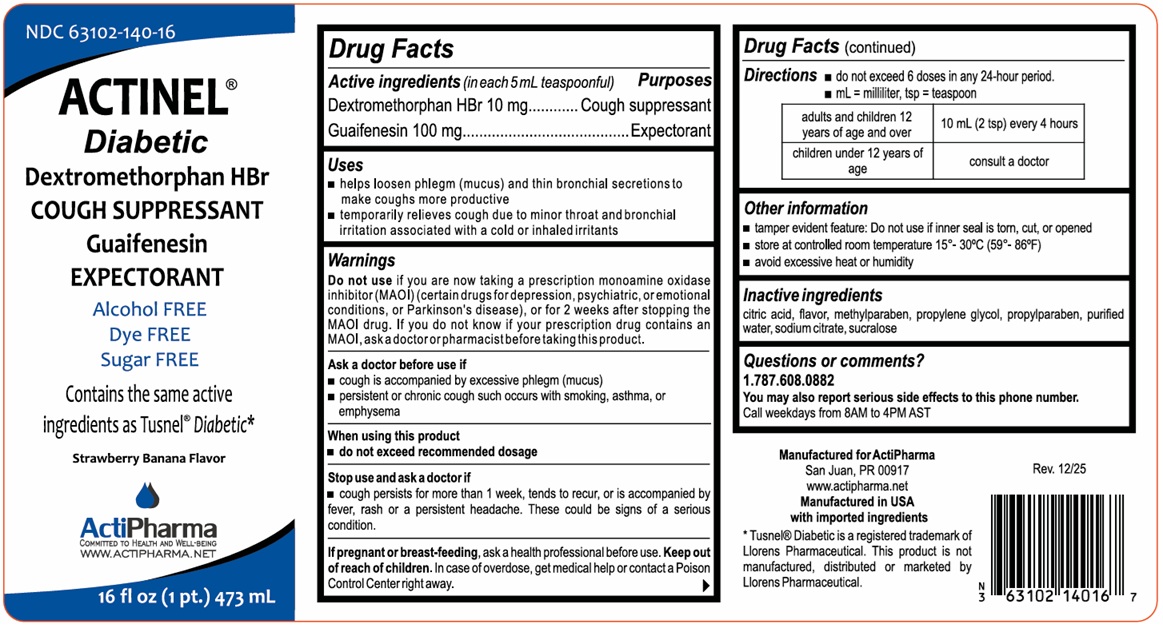 DRUG LABEL: ACTINEL Diabetic
NDC: 63102-140 | Form: LIQUID
Manufacturer: ACTIPHARMA, LLC
Category: otc | Type: HUMAN OTC DRUG LABEL
Date: 20260115

ACTIVE INGREDIENTS: DEXTROMETHORPHAN HYDROBROMIDE 10 mg/5 mL; GUAIFENESIN 100 mg/5 mL
INACTIVE INGREDIENTS: CITRIC ACID MONOHYDRATE; METHYLPARABEN; PROPYLENE GLYCOL; PROPYLPARABEN; WATER; SODIUM CITRATE, UNSPECIFIED FORM; SUCRALOSE

ACTINEL® Diabetic

Active ingredients (in each 5 mL teaspoonful)

Dextromethorphan HBr 10 mg

Guaifenesin 100 mg

Purposes

Cough suppressant

Expectorant

Uses

• helps loosen phlegm (mucus) and thin bronchial secretions to make coughs more productive

• temporarily relieves cough due to minor throat and bronchial irritation associated with a cold or inhaled irritants

Warnings

Do not use if you are now taking a prescription monoamine oxidase inhibitor (MAOI) (certain drugs for depression, psychiatric, or emotional conditions, or Parkinson's disease), or for 2 weeks after stopping the MAOI drug. If you do not know if your prescription drug contains an MAOI, ask a doctor or pharmacist before taking this product.

Ask a doctor before use if
• cough is accompanied by excessive phlegm (mucus)
• persistent or chronic cough such occurs with smoking, asthma, or emphysema

When using this product
• do not exceed recommended dosage

Stop use and ask a doctor if
• cough persists for more than 1 week, tends to recur, or is accompanied by fever, rash or a persistent headache, These could be signs of a serious condition.

If pregnant or breast-feeding, ask a health professional before use.

Keep out of reach of children. In case of overdose, get medical help or contact a Poison Control Center right away.

Directions

• do not exceed 6 doses in any 24-hour period.

• mL = milliliter, tsp = teaspoon

adults and children 12 years of age and over | 10 mL (2 tsp) every 4 hours
children under 12 years of age | consult a doctor

Other information

• tamper evident feature: Do not use if inner seal is torn, cut, or opened

• store at controlled room temperature 15° - 30°C (59° - 86°F)

• avoid excessive heat or humidity

Inactive ingredients

citric acid, flavor, methylparaben, propylene glycol, propylparaben, purified water, sodium citrate, sucralose

Questions or comments?

1.787.608.0082

You may also report serious side effects to this phone number.

Call weekdays from 8AM to 4PM AST

Alcohol FREE

Dye FREE

Sugar FREE

Contains the same active ingredients as Tusnel® Diabetic*

ActiPharma
COMMITTED TO HEALTH AND WELL-BEING
WWW.ACTIPHARMA.NET

Manufactured for ActiPharma
San Juan, PR 00917

Manufactured in USA with imported ingredients

*Tusnel® Diabetic is a registered trademark of Llorens Pharmaceutical. This product is not manufactured, distributed or marketed by Llorens Pharmaceutical.